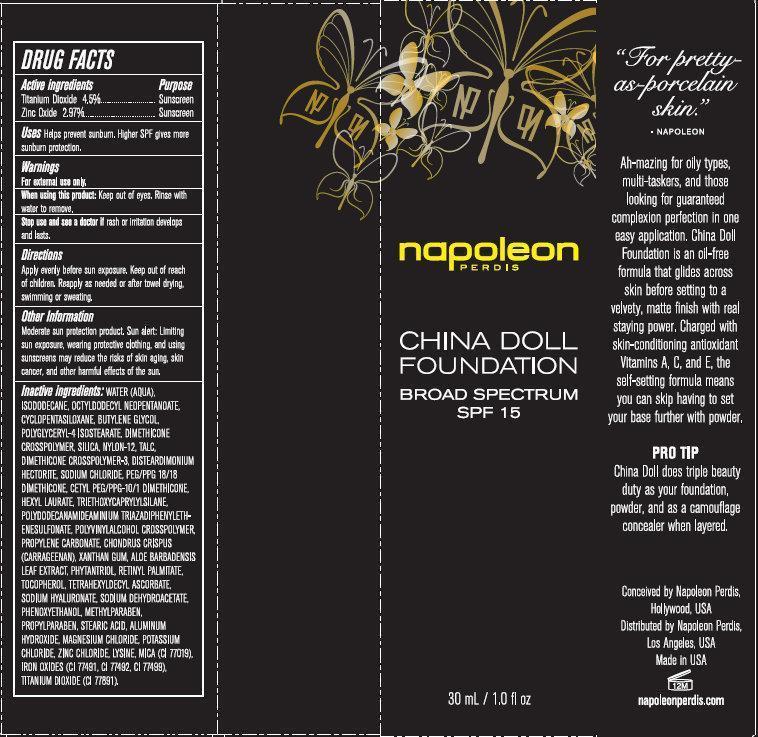 DRUG LABEL: CHINA DOLL FOUNDATION BROAD SPECTRUM SPF 15
NDC: 59735-500 | Form: CREAM
Manufacturer: MANA PRODUCTS, INC.
Category: otc | Type: HUMAN OTC DRUG LABEL
Date: 20240103

ACTIVE INGREDIENTS: ZINC OXIDE 2.97 g/100 g; TITANIUM DIOXIDE 4.5 g/100 g
INACTIVE INGREDIENTS: PHYTANTRIOL; VITAMIN A PALMITATE; TOCOPHEROL; TETRAHEXYLDECYL ASCORBATE; PHENOXYETHANOL; PROPYLPARABEN; FERRIC OXIDE RED; CYCLOMETHICONE 5; BUTYLENE GLYCOL; TALC; DISTEARDIMONIUM HECTORITE; HEXYL LAURATE; OCTYLDODECYL NEOPENTANOATE; POLYGLYCERYL-4 ISOSTEARATE; NYLON-12; SODIUM CHLORIDE; TRIETHOXYCAPRYLYLSILANE; CARRAGEENAN; LYSINE; MICA; FERROSOFERRIC OXIDE; WATER; ISODODECANE; SILICON DIOXIDE; PEG/PPG-18/18 DIMETHICONE; PROPYLENE CARBONATE; XANTHAN GUM; ALOE VERA LEAF; FERRIC OXIDE YELLOW; HYALURONATE SODIUM; SODIUM DEHYDROACETATE; METHYLPARABEN; STEARIC ACID; ALUMINUM HYDROXIDE; MAGNESIUM CHLORIDE; POTASSIUM CHLORIDE; ZINC CHLORIDE

CHINA DOLL FOUNDATION BROAD SPECTRUM SPF 15

Active ingredients

Titanium Dioxide 4.5%
Zinc Oxide 2.97%

Purpose

Sunscreen

Uses

Helps prevent sunburn. Higher SPF gives more sunburn protection.

Warnings

For external use only.

When using this product:

keep out of eyes. Rinse with water to remove.

Stop use and see a doctor if

rash or irritation develops and lasts.

Directions

Apply evenly before sun exposure. Children under 6 months of age: ask a doctor. Reapply as needed or after towel drying, swimming or sweating.

Other Information

Moderate sun protection product. Sun alert: Limiting sun exposure, wearing protective clothing, and using sunscreens may reduce the risks of skin aging, skin cancer, and other harmful effects of the sun.

Inactive ingredients

WATER, (AQUA), ISODODECANE, OCTYLDODECYL NEOPENTANOATE, CYCLOPENTASILOXANE, BUTYLENE GLYCOL, POLYGLYCERYL-4 ISOSTEARATE, DIMETHICONE CROSSPOLYMER, SILICA, NYLON-12, TALC, DIMETHICONE CROSSPOLYMER-3, DISTEARDIMONIUM HECTORITE, SODIUM CHLORIDE, PEG/PPG 18/18 DIMETHICONE, CETYL PEG/PPG-10/1 DIMETHICONE, HEXYL LAURATE, TRIETHOXYCAPRYLYLSILANE, POLYDODECANAMIDEAMINIUM TRIAZADIPHENYLETHENESULFONATE, POLYVINYLALCOHOL CROSSPOLYMER, PROPYLENE CARBONATE, CHONDRUS CRISPUS (CARRAGEENAN), XANTHAN GUM, ALOE BARBADENSIS LEAF EXTRACT, PHYTANTRIOL, RETINYL PALMITATE, TOCOPHEROL, TETRAHEXYLDECYL ASCORBATE, SODIUM HYALURONATE, SODIUM DEHYDROACETATE, PHENOXYETHANOL, METHYLPARABEN, PROPYLPARABEN, STEARIC ACID, ALUMINUM HYDROXIDE, MAGNESIUM CHLORIDE, POTASSIUM CHLORIDE, ZINC CHLORIDE, LYSINE, MICA (CI 77019), IRON OXIDES (CI 77491, CI 77492, CI 77499), TITANIUM DIOXIDE (CI 77891).

Stop use and ask a doctor if rash occurs.

RECENT MAJOR CHANGES

Dosage & Admin update

Keep out of reach of children. If product is swallowed, get medical help or contact a Poison Control Center right away.